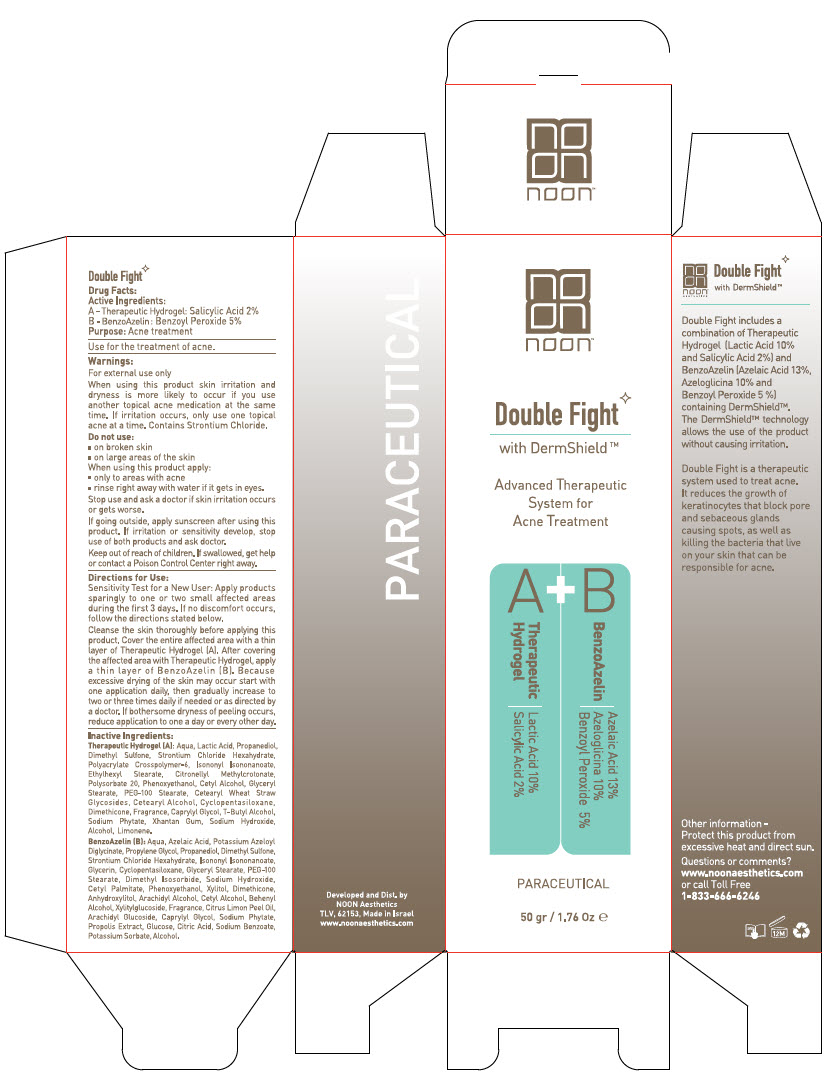 DRUG LABEL: Double Fight
NDC: 78863-1040 | Form: KIT | Route: TOPICAL
Manufacturer: Noon Aesthetics M.R. Ltd
Category: otc | Type: HUMAN OTC DRUG LABEL
Date: 20250113

ACTIVE INGREDIENTS: Salicylic Acid 0.5 g/25 g; Benzoyl Peroxide 1.25 g/25 g
INACTIVE INGREDIENTS: Polysorbate 20; Propanediol; Water; PHYTATE SODIUM; Dimethyl Sulfone; Strontium Chloride Hexahydrate; Xanthan Gum; AMMONIUM ACRYLOYLDIMETHYLTAURATE, DIMETHYLACRYLAMIDE, LAURYL METHACRYLATE AND LAURETH-4 METHACRYLATE COPOLYMER, TRIMETHYLOLPROPANE TRIACRYLATE CROSSLINKED (45000 MPA.S); TERT-BUTYL ALCOHOL; LACTIC ACID, DL-; Sodium Hydroxide; Cetearyl Wheat Straw Glycosides; CETOSTEARYL ALCOHOL; Isononyl Isononanoate; OCTYL STEARATE; Cetyl Alcohol; GLYCERYL MONOSTEARATE; PEG-100 Stearate; Phenoxyethanol; Caprylyl Glycol; Citronellyl Methylcrotonate; CYCLOMETHICONE 5; Dimethicone; Propanediol; Propylene Glycol; Azelaic Acid; Water; Sodium Hydroxide; Alcohol; ALPHA-ARBUTIN; Dimethyl Sulfone; STRONTIUM CHLORIDE HEXAHYDRATE; Glycerin; Arachidyl Alcohol; Arachidyl Glucoside; ANHYDROUS DEXTROSE; GLYCERYL MONOSTEARATE; PEG-100 STEARATE; Cetyl Palmitate; Dimethyl Isosorbide; Cetyl Alcohol; ISONONYL ISONONANOATE; Phenoxyethanol; Caprylyl Glycol; DOCOSANOL; CYCLOMETHICONE 5; Dimethicone; Xylitylglucoside; Anhydroxylitol; Xylitol; PROPOLIS WAX; CITRIC ACID MONOHYDRATE; Sodium Benzoate; Potassium Sorbate; PUMMELO; LEMON OIL, COLD PRESSED; PHYTATE SODIUM; POTASSIUM AZELOYL DIGLYCINATE

Double Fight

Drug Facts:

Active Ingredients

A - Therapeutic Hydrogel: Salicylic Acid 2%

B - Azelaic Cream: Benzoyl Peroxide 5%

Purpose

Acne treatment

INDICATIONS AND USAGE

Use for the treatment of acne.

Warnings

For external use only

When using this product skin irritation and dryness is more likely to occur if you use another topical acne medication at the same time. If irritation occurs, only use one topical acne at a time.

Do not use

- on broken skin
- on large areas of the skin

When using this product apply

- only to areas with acne
- rinse right away with water if it gets in eyes.

Stop use and ask a doctor if skin irritation occurs or gets worse.

If going outside, apply sunscreen after using this product. If irritation or sensitivity develop, stop use of both products and ask doctor.

Keep out of reach of children. If swallowed, get help or contact a Poison Control Center right away.

Directions

Sensitivity Test for a New User: Apply products sparingly to one or two small affected areas during the ﬁrst 3 days. If no discomfort occurs, follow the directions stated below.

Cleanse the skin thoroughly before applying this product. Cover the entire affected area with a thin layer of Therapeutic Hydrogel (A). After covering the affected area with Therapeutic Hydrogel, apply a thin layer of Azelaic Cream (B) Because excessive drying of the skin may occur start with one application daily, then gradually increase to two or three times daily if needed or as directed by a doctor. If bothersome dryness of peeling occurs, reduce application to one a day or every other day.

Inactive Ingredients

Therapeutic Hydrogel (A) Aqua, Lactic Acid, Propanediol, Dimethyl Sulfone, Strontium Chloride Hexahydrate, Polyacrylate Crosspolymer-6, Isononyl Isononanoate, Ethylhexyl Stearate, Citronellyl Methylcrotonate, Polysorbate 20, Phenoxyethanol, Cetyl Alcohol, Glyceryl Stearate, PEG-100 Stearate, Cetearyl Wheat Straw Glycosides, Cetearyl Alcohol, Cyclopentasiloxane ,Dimethicone, Parfum, Caprylyl Glycol, T-Butyl Alcohol, Sodium Phytate, Xhantan Gum, Sodium Hydroxide, Alcohol, Limonene.

Azelaic Cream (B) Aqua, Azelaic Acid, Azeloglicina, Propylene Glycol, Propanediol, Dimethyl Sulfone, Strontium Chloride Hexahydrate, Alpha-Arbutin, Isononyl Isononanoate, Glycerin, Cyclopentasiloxane, Glyceryl Stearate, PEG-100 Stearate, Dimethyl Isosorbide, Sodium Hydroxide, Cetyl Palmitate, Phenoxyethanol, Xylitol, Dimethicone, Anhydroxylitol, Arachidyl Alcohol, Cetyl Alcohol, Behenyl Alcohol, Xylitylglucoside, Parfum, Citrus Limon Peel Oil, Arachidyl Glucoside, Caprylyl Glycol, Sodium Phytate, Propolis Extract, Glucose, Citric Acid, Sodium Benzoate, Potassium Sorbate, Alcohol.

Other information

Protect this product from excessive heat and direct sun.

Questions or comments?

www.noonaesthetics.com or call Toll Free 1-833-666-6246

Developed and Dist. by
NOON Aesthetics
TLV, 62153

PRINCIPAL DISPLAY PANEL - Kit Carton

noon™

Double Fight

with DermShield™

Advanced Therapeutic
System for
Acne Treatment

A
Therapeutic
Hydrogel
Lactic Acid 10%
Salicylic Acid 2%

+

B
BenzoAzelin
Azelaic Acid 13%
Azeloglicina 10%
Benzoyl Peroxide 5%

PARACEUTICAL

50 gr / 1.76 Oz ℮